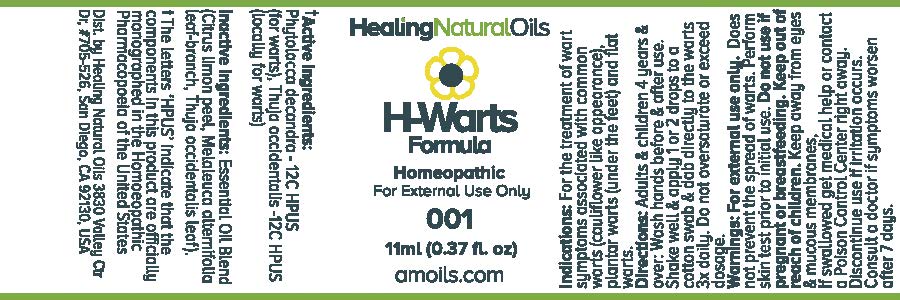 DRUG LABEL: H-Warts Formula
NDC: 61077-001 | Form: OIL
Manufacturer: Healing Natural Oils
Category: homeopathic | Type: HUMAN OTC DRUG LABEL
Date: 20171211

ACTIVE INGREDIENTS: PHYTOLACCA AMERICANA ROOT 12 [hp_C]/11 mL; THUJA OCCIDENTALIS LEAFY TWIG 12 [hp_C]/11 mL
INACTIVE INGREDIENTS: LEMON PEEL; MELALEUCA ALTERNIFOLIA LEAF; THUJA OCCIDENTALIS LEAF

Active Ingredients:

Phytolacca decandra - 12C HPUS
Thuja occidentalis -12C HPUS

Purpose

Phytolacca decandra -12C HPUS (for warts),

Thuja occidentalis -12C HPUS (locally for warts)

The letters ‘HPUS’ indicate that the components in this product are officially monographed in the Homoeopathic Pharmacopoeia of the United States

Inactive Ingredients:

Essential Oil Blend (Citrus limon peel, Melaleuca alternifolia leaf-branch, Thuja occidentalis leaf)

Indications:

For the treatment of wart symptoms associated with common warts (cauliflower like appearance), plantar warts (under the feet) and flat warts.

Directions:

Adults and children 4 years and over: Wash hands before and after use.
Shake well and apply 1 or 2 drops to a cotton swab and dab directly to the warts 3x daily.
Do not oversaturate or exceed dosage.

Warnings:

For external use only.
Does not prevent the spread of warts. Perform skin test prior to initial use.

Do not use if pregnant or breastfeeding.

Keep out of reach of children.

OTHER SAFETY INFORMATION

Keep away from eyes and mucous membranes. If swallowed get medical help or contact a Poison Control
Center right away.

Discontinue use if irritation occurs.

ASK DOCTOR

Consult a doctor if symptoms worsen after 7 days.

DESCRIPTION

Dist. by Healing Natural Oils 3830 Valley Ctr Dr, #705-526, San Diego, CA 92130, USA

PACKAGE LABEL

Healing Natural Oils

H-Warts
Formula

Homeopathic
For External Use Only

001

11ml (0.37 fl. oz)
amoils.com